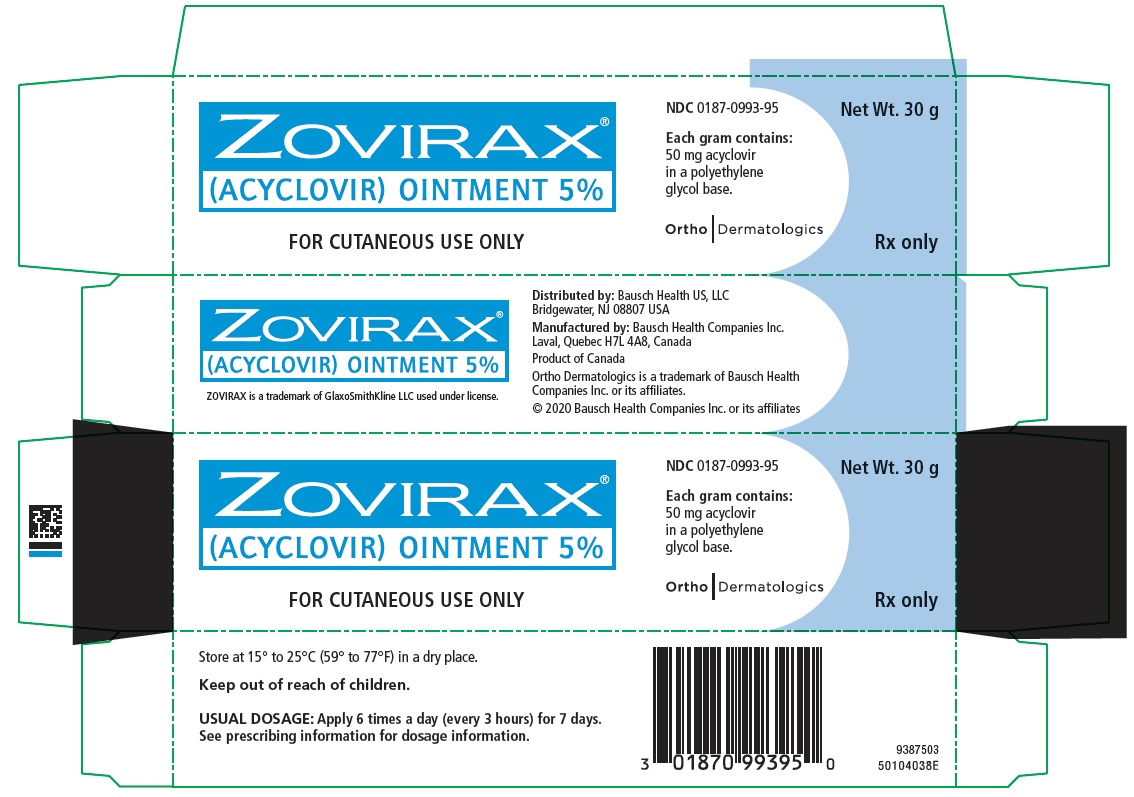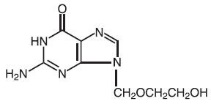 DRUG LABEL: Zovirax
NDC: 0187-0993 | Form: OINTMENT
Manufacturer: Bausch Health US, LLC
Category: prescription | Type: HUMAN PRESCRIPTION DRUG LABEL
Date: 20201031

ACTIVE INGREDIENTS: acyclovir 50 mg/1 g
INACTIVE INGREDIENTS: POLYETHYLENE GLYCOL, UNSPECIFIED

PRESCRIBING INFORMATION
ZOVIRAX®
(acyclovir)
Ointment 5%

DESCRIPTION

ZOVIRAX is the brand name for acyclovir, a synthetic nucleoside analogue active against herpes viruses. ZOVIRAX Ointment 5% is a formulation for topical administration. Each gram of ZOVIRAX Ointment 5% contains 50 mg of acyclovir in a polyethylene glycol (PEG) base.

Acyclovir is a white to off-white crystalline powder with the molecular formula C8H11N5O3 and a molecular weight of 225.20. The maximum solubility in water at 37°C is 2.5 mg/mL. The pka’s of acyclovir are 2.27 and 9.25.

The chemical name of acyclovir is 2-amino-1,9-dihydro-9-[(2-hydroxyethoxy)methyl]-6H-purin-6-one; it has the following structural formula:

VIROLOGY

Mechanism of Antiviral Action: Acyclovir is a synthetic purine nucleoside analogue with in vitro and in vivo inhibitory activity against herpes simplex virus types 1 (HSV-1), 2 (HSV-2), and varicella zoster virus (VZV).

The inhibitory activity of acyclovir is highly selective due to its affinity for the enzyme thymidine kinase (TK) encoded by HSV and VZV. This viral enzyme converts acyclovir into acyclovir monophosphate, a nucleotide analogue. The monophosphate is further converted into diphosphate by cellular guanylate kinase and into triphosphate by a number of cellular enzymes. In vitro, acyclovir triphosphate stops replication of herpes viral DNA. This is accomplished in three ways: 1) competitive inhibition of viral DNA polymerase, 2) incorporation into and termination of the growing viral DNA chain, and 3) inactivation of the viral DNA polymerase. The greater antiviral activity of acyclovir against HSV compared to VZV is due to its more efficient phosphorylation by the viral TK.

Antiviral Activities: The quantitative relationship between the in vitro susceptibility of herpes viruses to antivirals and the clinical response to therapy has not been established in humans, and virus sensitivity testing has not been standardized. Sensitivity testing results, expressed as the concentration of drug required to inhibit by 50% the growth of virus in cell culture (IC50), vary greatly depending upon a number of factors. Using plaque-reduction assays, the IC50 against HSV isolates ranges from 0.02 to 13.5 mcg/mL for HSV-1 and from 0.01 to 9.9 mcg/mL for HSV-2. The IC50 for acyclovir against most laboratory strains and clinical isolates of VZV ranges from 0.12 to 10.8 mcg/mL. Acyclovir also demonstrates activity against the Oka vaccine strain of VZV with a mean IC50 of 1.35 mcg/mL.

Drug Resistance: Resistance of HSV and VZV to acyclovir can result from qualitative and quantitative changes in the viral TK and/or DNA polymerase. Clinical isolates of HSV and VZV with reduced susceptibility to acyclovir have been recovered from immunocompromised patients, especially with advanced HIV infection. While most of the acyclovir-resistant mutants isolated thus far from immunocompromised patients have been found to be TK-deficient mutants, other mutants involving the viral TK gene (TK partial and TK altered) and DNA polymerase have been isolated. TK-negative mutants may cause severe disease in infants and immunocompromised adults. The possibility of viral resistance to acyclovir should be considered in patients who show poor clinical response during therapy.

CLINICAL PHARMACOLOGY

Two clinical pharmacology studies were performed with ZOVIRAX Ointment 5% in immunocompromised adults at risk of developing mucocutaneous HSV infections or with localized varicella zoster infections. These studies were designed to evaluate the dermal tolerance, systemic toxicity, and percutaneous absorption of acyclovir.

In one of these studies, which included 16 inpatients, the complete ointment or its vehicle were randomly administered in a dose of 1-cm strips (25 mg acyclovir) 4 times a day for 7 days to an intact skin surface area of 4.5 square inches. No local intolerance, systemic toxicity, or contact dermatitis were observed. In addition, no drug was detected in blood and urine by radioimmunoassay (sensitivity, 0.01 mcg/mL).

The other study included 11 patients with localized varicella zoster infections. In this uncontrolled study, acyclovir was detected in the blood of 9 patients and in the urine of all patients tested. Acyclovir levels in plasma ranged from <0.01 to 0.28 mcg/mL in 8 patients with normal renal function, and from <0.01 to 0.78 mcg/mL in one patient with impaired renal function. Acyclovir excreted in the urine ranged from <0.02% to 9.4% of the daily dose. Therefore, systemic absorption of acyclovir after topical application is minimal.

CLINICAL TRIALS

In clinical trials of initial genital herpes infections, ZOVIRAX Ointment 5% has shown a decrease in healing time and, in some cases, a decrease in duration of viral shedding and duration of pain. In studies in immunocompromised patients primarily with herpes labialis, there was a decrease in duration of viral shedding and a slight decrease in duration of pain.

In studies of recurrent genital herpes and of herpes labialis in nonimmunocompromised patients, there was no evidence of clinical benefit; there was some decrease in duration of viral shedding.

INDICATIONS AND USAGE

ZOVIRAX Ointment 5% is indicated in the management of initial genital herpes and in limited non-lifethreatening mucocutaneous HSV infections in immunocompromised patients.

CONTRAINDICATIONS

ZOVIRAX Ointment 5% is contraindicated in patients who develop hypersensitivity to the components of the formulation.

WARNINGS

ZOVIRAX Ointment 5% is intended for cutaneous use only and should not be used in the eye.

PRECAUTIONS

GENERAL PRECAUTIONS

General: The recommended dosage, frequency of applications, and length of treatment should not be exceeded (see DOSAGE AND ADMINISTRATION). There are no data to support the use of ZOVIRAX Ointment 5% to prevent transmission of infection to other persons or prevent recurrent infections when applied in the absence of signs and symptoms. ZOVIRAX Ointment 5% should not be used for the prevention of recurrent HSV infections. Although clinically significant viral resistance associated with the use of ZOVIRAX Ointment 5% has not been observed, this possibility exists.

DRUG INTERACTIONS

Drug Interactions: Clinical experience has identified no interactions resulting from topical or systemic administration of other drugs concomitantly with ZOVIRAX Ointment 5%.

CARCINOGENESIS AND MUTAGENESIS AND IMPAIRMENT OF FERTILITY

Carcinogenesis, Mutagenesis, Impairment of Fertility: Systemic exposure following topical administration of acyclovir is minimal. Dermal carcinogenicity studies were not conducted. Results from the studies of carcinogenesis, mutagenesis, and fertility are not included in the full prescribing information for ZOVIRAX Ointment 5% due to the minimal exposures of acyclovir that result from dermal application. Information on these studies is available in the full prescribing information for ZOVIRAX Capsules, Tablets, and Suspension and ZOVIRAX for Injection.

PREGNANCY

TERATOGENIC EFFECTS

Pregnancy: Teratogenic Effects: Acyclovir was not teratogenic in the mouse, rabbit, or rat at exposures greatly in excess of human exposure. There are no adequate and well-controlled studies of systemic acyclovir in pregnant women. A prospective epidemiologic registry of acyclovir use during pregnancy was established in 1984 and completed in April 1999. There were 749 pregnancies followed in women exposed to systemic acyclovir during the first trimester of pregnancy resulting in 756 outcomes. The occurrence rate of birth defects approximates that found in the general population. However, the small size of the registry is insufficient to evaluate the risk for less common defects or to permit reliable or definitive conclusions regarding the safety of acyclovir in pregnant women and their developing fetuses. Systemic acyclovir should be used during pregnancy only if the potential benefit justifies the potential risk to the fetus.

NURSING MOTHERS

Nursing Mothers: It is not known whether topically applied acyclovir is excreted in breast milk. Systemic exposure following topical administration is minimal. After oral administration of ZOVIRAX, acyclovir concentrations have been documented in breast milk in two women and ranged from 0.6 to 4.1 times the corresponding plasma levels. These concentrations would potentially expose the nursing infant to a dose of acyclovir up to 0.3 mg/kg/day. Nursing mothers who have active herpetic lesions near or on the breast should avoid nursing.

GERIATRIC USE

Geriatric Use: Clinical studies of ZOVIRAX Ointment did not include sufficient numbers of subjects aged 65 and over to determine whether they respond differently from younger subjects. Other reported clinical experience has not identified differences in responses between the elderly and younger patients. Systemic absorption of acyclovir after topical administration is minimal (see CLINICAL PHARMACOLOGY).

PEDIATRIC USE

Pediatric Use: Safety and effectiveness in pediatric patients have not been established.

ADVERSE REACTIONS

In the controlled clinical trials, mild pain (including transient burning and stinging) was reported by about 30% of patients in both the active and placebo arms; treatment was discontinued in two of these patients. Local pruritus occurred in 4% of these patients. In all studies, there was no significant difference between the drug and placebo group in the rate or type of reported adverse reactions nor were there any differences in abnormal clinical laboratory findings.

Observed During Clinical Practice: Based on clinical practice experience in patients treated with ZOVIRAX Ointment in the U.S., spontaneously reported adverse events are uncommon. Data are insufficient to support an estimate of their incidence or to establish causation. These events may also occur as part of the underlying disease process. Voluntary reports of adverse events that have been received since market introduction include:

General: Edema and/or pain at the application site.

Skin: Pruritus, rash.

To report SUSPECTED ADVERSE REACTIONS, contact Bausch Health US, LLC at 1-800-321-4576 or FDA at 1-800-FDA-1088 or www.fda.gov/medwatch.

OVERDOSAGE

Overdosage by topical application of ZOVIRAX Ointment 5% is unlikely because of limited transcutaneous absorption (see CLINICAL PHARMACOLOGY).

DOSAGE AND ADMINISTRATION

Apply sufficient quantity to adequately cover all lesions every 3 hours, 6 times per day for 7 days. The dose size per application will vary depending upon the total lesion area but should approximate a one-half inch ribbon of ointment per 4 square inches of surface area. A finger cot or rubber glove should be used when applying ZOVIRAX to prevent autoinoculation of other body sites and transmission of infection to other persons. Therapy should be initiated as early as possible following onset of signs and symptoms.

HOW SUPPLIED

Each gram of ZOVIRAX Ointment 5% contains 50 mg acyclovir in a polyethylene glycol base. It is supplied as follows:

30 g tubes NDC 0187-0993-95

STORAGE AND HANDLING

Store at 15° to 25°C (59° to 77°F) in a dry place.

Distributed by:
Bausch Health US, LLC
Bridgewater, NJ 08807 USA

Manufactured by:
Bausch Health Companies Inc.
Laval, Quebec H7L 4A8, Canada

ZOVIRAX is a trademark of GlaxoSmithKline LLC used under license.

© 2020 Bausch Health Companies Inc. or its affiliates

Rev. 10/2020

9462302

PRINCIPAL DISPLAY PANEL - 30 g Tube Carton

ZOVIRAX®
(ACYCLOVIR) OINTMENT 5%

FOR CUTANEOUS USE ONLY

NDC 0187-0993-95

Net Wt. 30 g

Each gram contains:
50 mg acyclovir
in a polyethylene
glycol base.

Ortho Dermatologics

Rx only